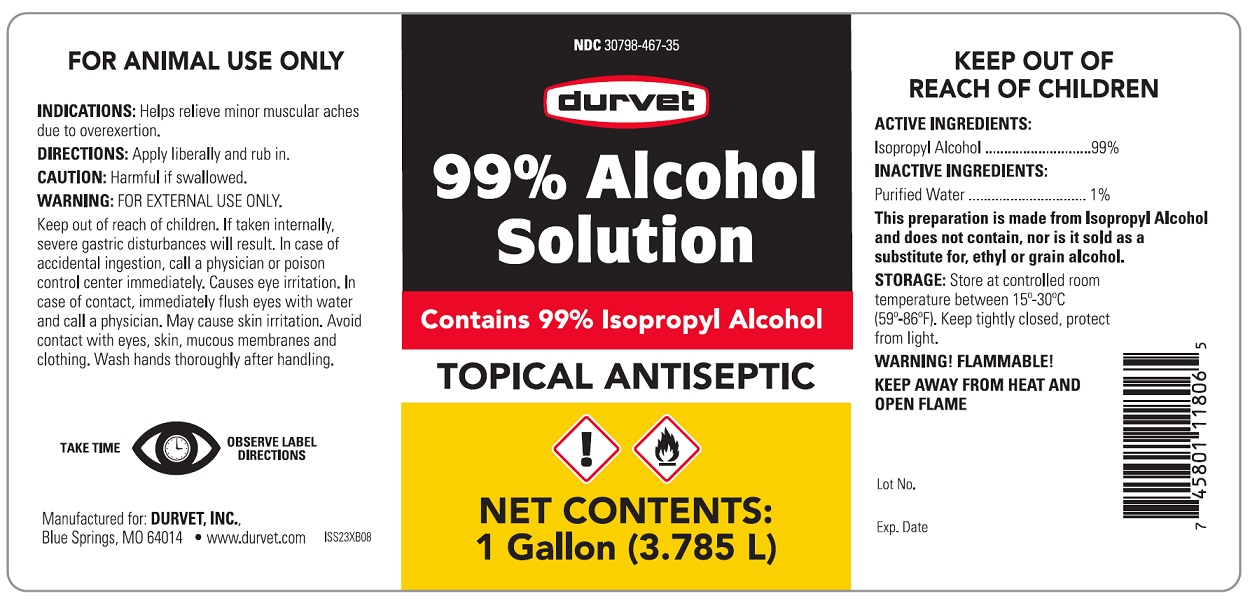 DRUG LABEL: ISOPROPYL ALCOHOL
NDC: 30798-467 | Form: LIQUID
Manufacturer: Durvet, Inc
Category: animal | Type: OTC ANIMAL DRUG LABEL
Date: 20241028

ACTIVE INGREDIENTS: ISOPROPYL ALCOHOL 99 L/100 L
INACTIVE INGREDIENTS: WATER 1 L/100 L

INDICATIONS AND USAGE

99% Alcohol Solution

Conatins 99% Isopropyl Alcohol

Topical Antiseptic

Net Contents: 1 Gallon (3.785 L)

FOR ANIMAL USE ONLY

KEEP OUT OF REACH OF CHILDREN

INDICATIONS: Helps relieve minor muscular aches due to overexertion.

DIRECTIONS

Apply liberally and rub in.

CAUTION

Harmful if swallowed.

WARNING

FOR EXTERNAL USE ONLY. Keep out of reach of children. If taken internally sever gastric disturbances will result. In case of accidental ingestion, call a physician or poison control center immediately. Causes eye irritation. In case of contact, immediately flush eyes with water and call a physician. May cause skin irritation. Avoid contact with eyes, skin, mucous membranes and clothing. Wash hands thoroughly after handling.

WARNING! FLAMMABLE! KEEP AWAY FROM HEAT AND OPEN FLAME

DESCRIPTION

ACTIVE INGREDIENTS
Isopropyl Alcohol ...............99%

INACTIVE INGREDIENTS
Purified Water .................. 1%

This preparation is made from Isopropyl Alcohol and does not contain, nor is it sold as a substitute for, ethyl or grain alcohol.

STORAGE

Store at controlled room temperature between 15o-30oC (59o-86oF). Keep tightly closed, protect from sunlight.